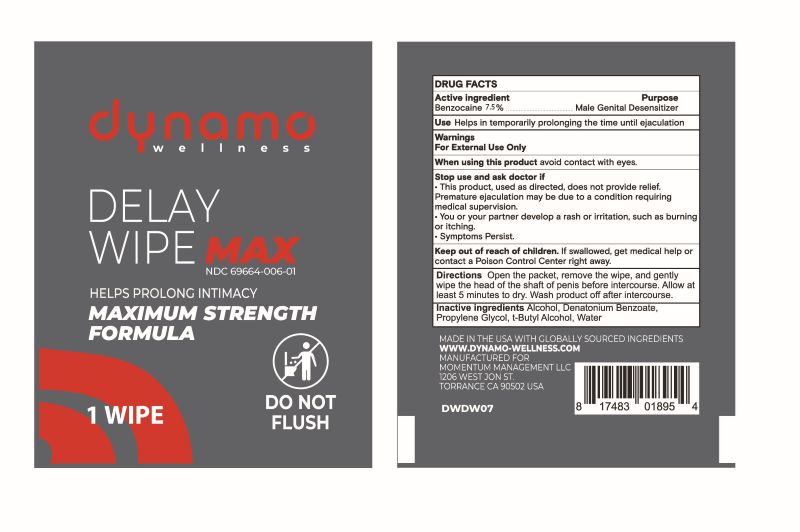 DRUG LABEL: Dynamo Wellness Delay MAX Wipe
NDC: 69664-006 | Form: CLOTH
Manufacturer: Momentum Management LLC
Category: otc | Type: Human OTC Drug Label
Date: 20260128

ACTIVE INGREDIENTS: BENZOCAINE 7.5 g/100 g
INACTIVE INGREDIENTS: ALCOHOL; DENATONIUM BENZOATE; PROPYLENE GLYCOL; BUTYL ALCOHOL; WATER

Dynamo Wellness Delay MAX Wipe
Momentum Management LLC

PURPOSE

External Analgesic

USE(S)

Helps in temporarily prolonging the time until ejaculation.

WARNINGS

- For external use only.
- When using this product, avoid contact with eyes.

STOP USE AND ASK DOCTOR IF

- This product, used as directed, does not provide relief. Premature ejaculation may be due to a condition requiring medical supervision.
- You or your partner develop a rash or irritation, such as burning or itching.
- Symptoms persist.

KEEP OUT OF REACH OF CHILDREN

If swallowed, get medical help or contact a Poison Control Center right away.

INACTIVE INGREDIENTS

Alcohol, Denatonium Benzoate, Propylene Glycol, t-Butyl Alcohol, Water.

DIRECTIONS

Open the packet, remove the wipe, and gently wipe the head of the shaft of penis before intercourse. Allow at least 5 minutes to dry. Wash product off after intercourse.

PRINCIPAL DISPLAY PANEL

- Package Type: Individually Wrapped Wipe
- Quantity: 1 wipe per package
- Size: 2.375 inch x 3 inch foil

Manufacturer Information

Momentum Management LLC

1206 West Jon Street

Torrance, CA. 90502

+1 310 446-1632